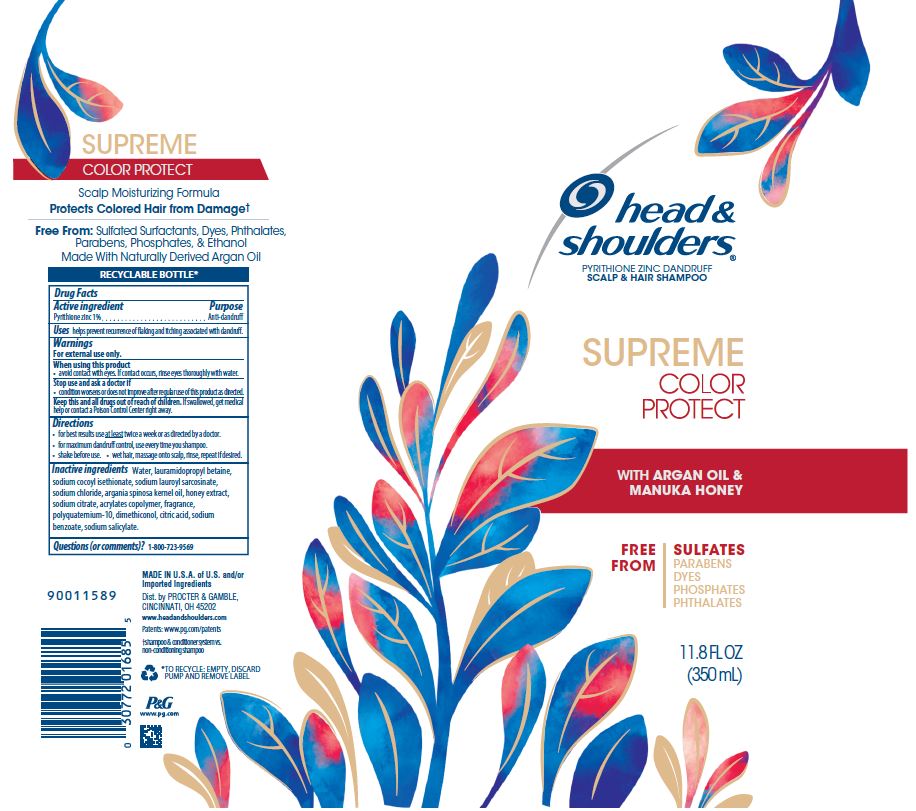 DRUG LABEL: Head and Shoulders Supreme Color Protect
NDC: 69423-346 | Form: SHAMPOO
Manufacturer: The Procter & Gamble Manufacturing Company
Category: otc | Type: HUMAN OTC DRUG LABEL
Date: 20251218

ACTIVE INGREDIENTS: PYRITHIONE ZINC 1 g/100 mL
INACTIVE INGREDIENTS: SODIUM LAUROYL SARCOSINATE; WATER; SODIUM CHLORIDE; LAURAMIDOPROPYL BETAINE; HONEY; DIMETHICONOL (50000 CST); ARGAN OIL; POLYQUATERNIUM-10 (30000 MPA.S AT 2%); SODIUM COCOYL ISETHIONATE; SODIUM BENZOATE; CITRIC ACID MONOHYDRATE; SODIUM CITRATE; LAURETH-23; TRIETHANOLAMINE DODECYLBENZENESULFONATE; SODIUM SALICYLATE

Head and Shoulders® Supreme Color Protect Shampoo

Drug Facts

Active ingredient

Pyrithione zinc 1%

Purpose

Anti-dandruff

Uses

helps prevent recurrence of flaking and itching associated with dandruff.

Warnings

For external use only.

When using this product

- avoid contact with eyes. If contact occurs, rinse eyes thoroughly with water.

Stop use and ask a doctor if

- condition worsens or does not improve after regular use of this product as directed.

KEEP OUT OF REACH OF CHILDREN

Keep this and all drugs out of reach of children. If swallowed, get medical help or contact a Poison Control Center right away.

Directions

- for best results use at least twice a week or as directed by a doctor.
- for maximum dandruff control, use every time you shampoo.
- shake before use.
- wet hair, massage onto scalp, rinse, repeat if desired.

Inactive Ingredients

Water, lauramidopropyl betaine, sodium cocoyl isethionate, sodium lauroyl sarcosinate, sodium chloride, argania spinosa kernel oil, honey extract, sodium citrate, acrylates copolymer, fragrance, polyquaternium-10, dimethiconol, citric acid, sodium benzoate, sodium salicylate.

Questions (or comments)?

1-800-723-9569

Dist. by PROCTER & GAMBLE,
CINCINNATI, OH 45202

PRINCIPAL DISPLAY PANEL - 350 mL Bottle Label

head &
shoulders®
PYRITHIONE ZINC DANDRUFF

SCALP & HAIR SHAMPOO

SUPREME

COLOR

PROTECT

WITH ARGAN OIL

& MANUKA HONEY

FREE FROM

SULFATES PHOSPHATES

PARABENS

PHTHALATES

DYES

11.8 FL OZ
(350 mL)